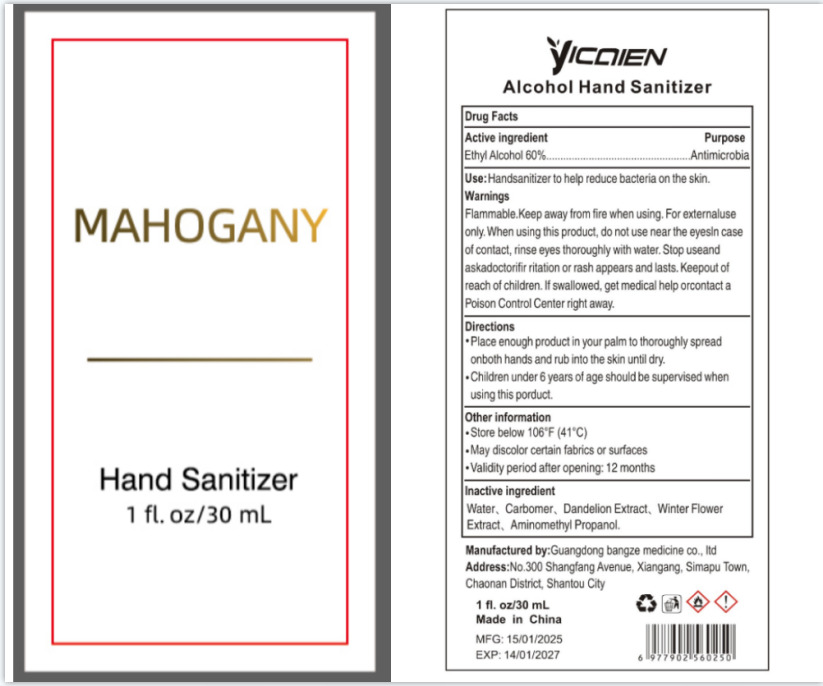 DRUG LABEL: Alcohol Hand Sanitizer
NDC: 85279-001 | Form: LIQUID
Manufacturer: Guangdong bangze medicine co., ltd
Category: otc | Type: HUMAN OTC DRUG LABEL
Date: 20260114

ACTIVE INGREDIENTS: ALCOHOL 60 g/100 mL
INACTIVE INGREDIENTS: CARBOMER; WATER; TARAXACUM OFFICINALE (DANDELION) ROOT; AMINOMETHYL PROPANOL; TUSSILAGO FARFARA LEAF

85279-001
Alcohol Hand Sanitizer

Active Ingredient(s)

Ethyl Alcohol 60%

Purpose

Antimicrobia

Use

Handsanitizer to help reduce bacteria on the skin.

Warnings

For external use only.

Do not use near the eyesIn case of contact, rinse eyes thoroughly with water.

When using this product, do not use near the eyesln case of contact, rinse eyes thoroughly with water.

STOP USE

Stop useand askadoctorifir ritation or rash appears and lasts.

KEEP OUT OF REACH OF CHILDREN

Keepout of reach of children. If swallowed, get medical help orcontacta
Poison Control Center right away.

Directions

●Place enough product in your palm to thoroughly spread
onboth hands and rub into the skin until dry.
●Children under 6 years of age should be supervised when
using this porduct.

Other information

●Store below 106'F (41°C)
●May discolor certain fabrics or surfaces
●Validity period after opening: 12 months

Inactive ingredients

Water, Carbomer, Dandelion Extract, Winter FlowerExtract, Aminomethyl Propanol